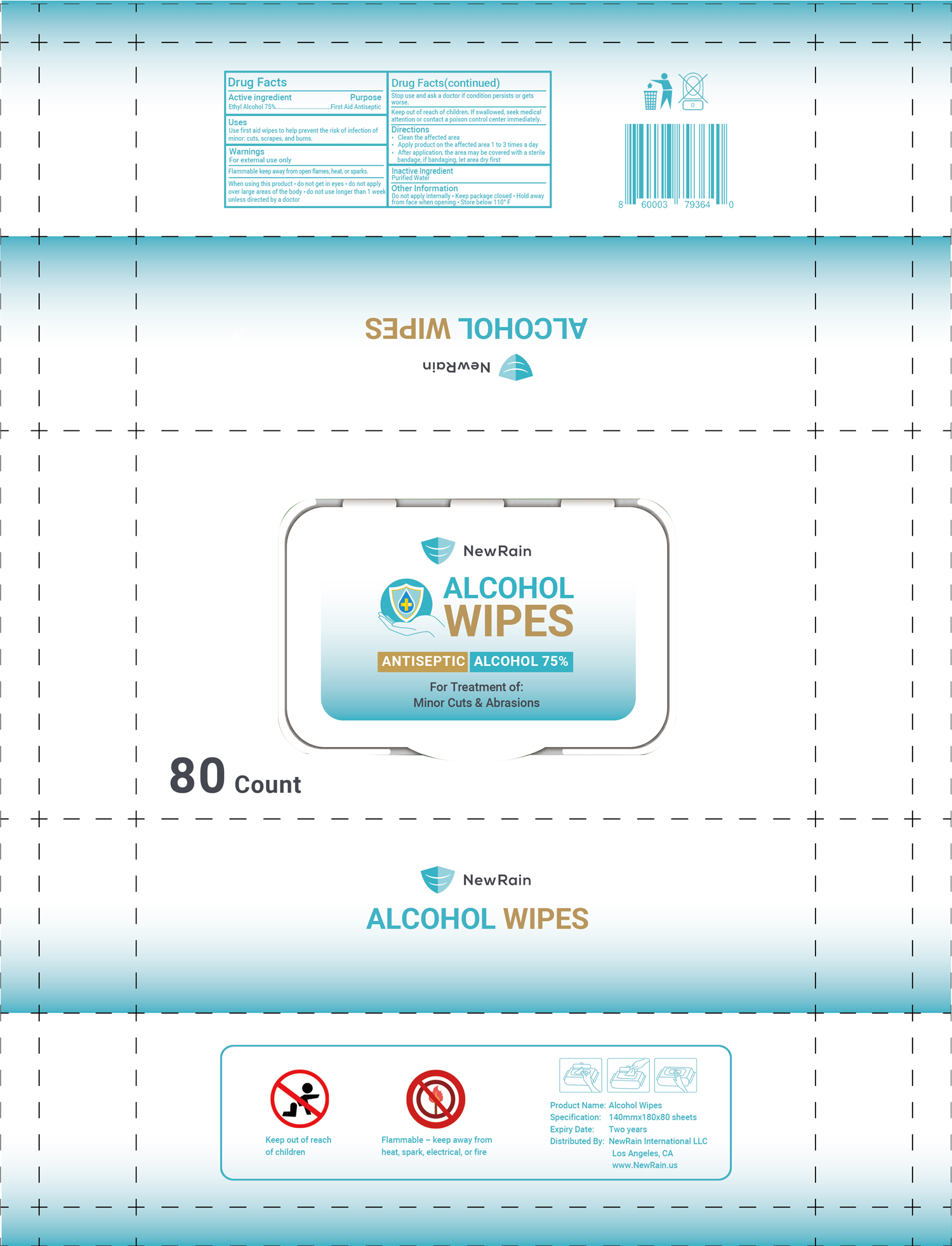 DRUG LABEL: NewRain Alcohol Wipes
NDC: 78150-007 | Form: CLOTH
Manufacturer: Zhejiang Yiwu Caijie Daily Necessities Factory
Category: otc | Type: HUMAN OTC DRUG LABEL
Date: 20200804

ACTIVE INGREDIENTS: ALCOHOL 75 mL/100 g
INACTIVE INGREDIENTS: WATER

NewRain Alcohol Wipes

Active Ingredient(s)

Alcohol 75%. Purpose: First Aid Antiseptic

Purpose

First Aid Antiseptic, Hand Sanitizer wipes

Use

Use first aid wipes to help prevent the risk of infection of minor: cuts, scrapes, and burns.

Warnings

For external use only

Flammable keep away from open flames, heat, or sparks.

When using this product

- do not get in eyes
- do not apply over large area of the body
- do not use longer than 1 week unless directed by a doctor

Stop use and ask a doctor if condition persists or gets worse.

KEEP OUT OF REACH OF CHILDREN

Keep our of reach of children. If swallowed, seek medical attention or contact a poison control center immediately.

Directions

- Clean the affected area
- Apply product on the affected area 1 to 3 times a day
- After application, the area may be covered with a sterile bandage, if bandaging, let area dry first.

Inactive ingredients

Purified water

Other information

- Do not apply internally.
- Keep package closed.
- Hold away from face when opening
- Store below 110F

Package Label - Principal Display Panel

80 PCS 78150-007-01